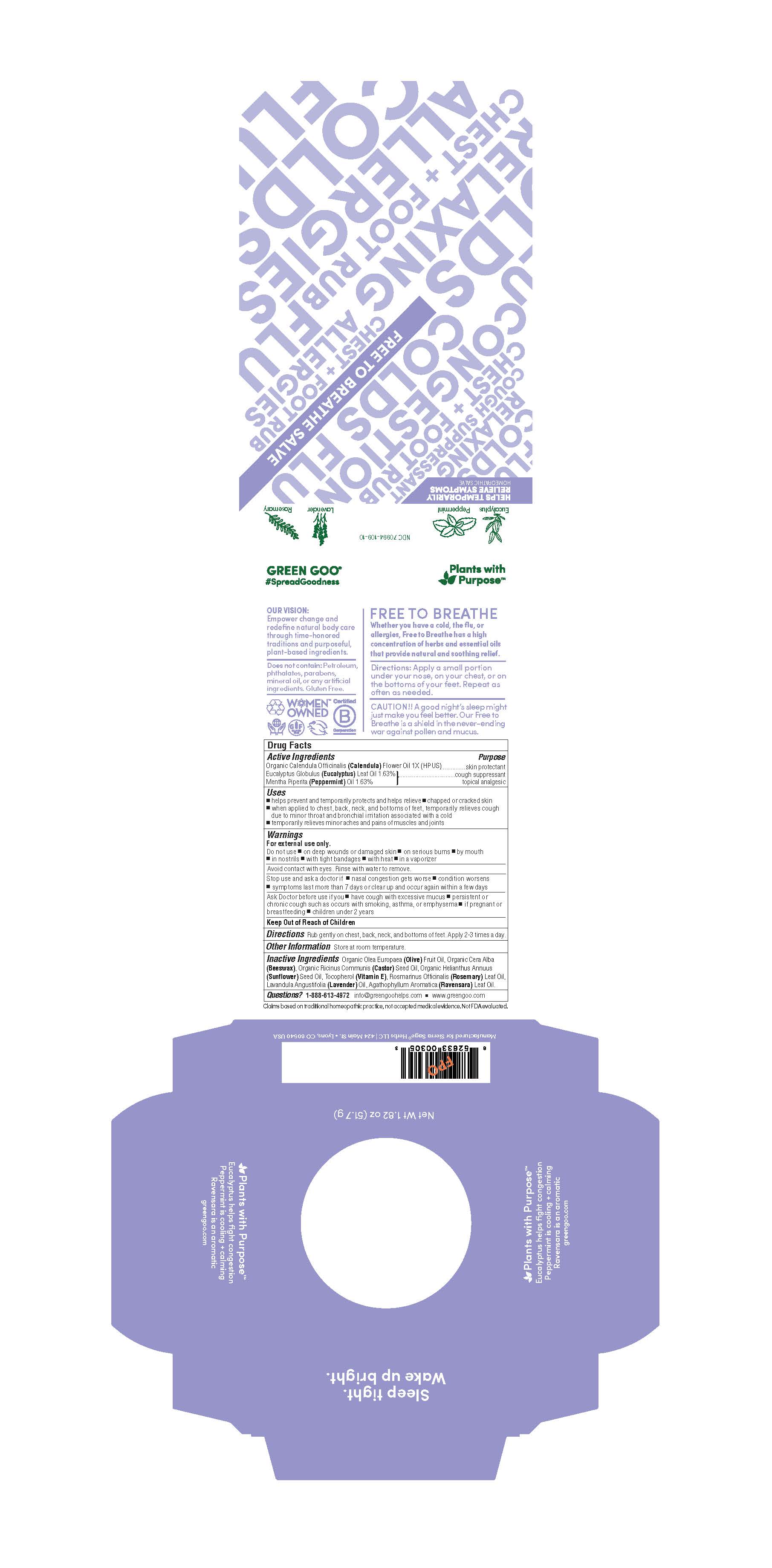 DRUG LABEL: Free to Breathe
NDC: 70994-109 | Form: SALVE
Manufacturer: Spry Life LLC
Category: homeopathic | Type: HUMAN OTC DRUG LABEL
Date: 20251215

ACTIVE INGREDIENTS: CALENDULA OFFICINALIS FLOWER 1 [hp_X]/100 g; EUCALYPTUS GLOBULUS LEAF 1.63 g/100 g; MENTHA PIPERITA 1.63 g/100 g
INACTIVE INGREDIENTS: SUNFLOWER OIL; LAVENDER OIL; CRYPTOCARYA AGATHOPHYLLA LEAF OIL; OLIVE OIL; ALPHA-TOCOPHEROL; ROSEMARY OIL; YELLOW WAX; CASTOR OIL

Free to Breathe

Purpose

Skin Protectant

Cough Suppressant

Topical Analgesic

OTC Active Ingredients

Organic Calendula Officinalis (Calendula) Flower Oil

Eucalyptus Globulus (Eucalyptus) Oil

Mentha Piperita (Peppermint) Oil

Indications & Usage

■ helps prevent and temporarily protects and helps relieve ■ chapped or cracked skin

■ when applied to the chest, throat, and bottom of feet, temporarily relieves cough due to minor throat and bronchial irritation associated with a cold

■ temporarily relieves minor aches and pains of muscles and joints

Warnings

For external use only.

Do not use on ■ on deep wounds ■ serious burns ■ by mouth ■ in nostrils ■ with tight bandages ■ with heat ■ in a vaporizor

Avoid contact with eyes. Rinse with water to remove eyes. Rinse with water to remove.

Stop use and ask a doctor if you ■ nasal congestion gets worse ■ condition worsens ■ symptoms last more than 7 days or clears up and occurs again within a few days

Ask Doctore before use if you ■ have cough with excessive mucus ■ persistent or chronic cough such as occurs with smoking, asthma, or emphysema ■ if pregnant or breast-feeding ■ children under 2 years

Keep Out of Reach of Children

Storage and Handling

Store at room temperature.

Dosage & Administration

Rub gently on chest, neck or bottom of the feet. Apply 2-3 times a day.

Inactive Ingredients

Organic Olea Europaea (Olive) Fruit Oil, Organic Cera Alba (Beeswax), Organic Ricinus Communis (Castor) Seed Oil, Organic Helianthus Annuus (Sunflower) Seed Oil, Tocopherol (Vitamin E), Rosmarinus Officinalis (Rosemary) Leaf Oil, Lavandula Angustifolia (Lavender) Oil, Agathophyllum Aromatica (Ravensara) Leaf Oil.